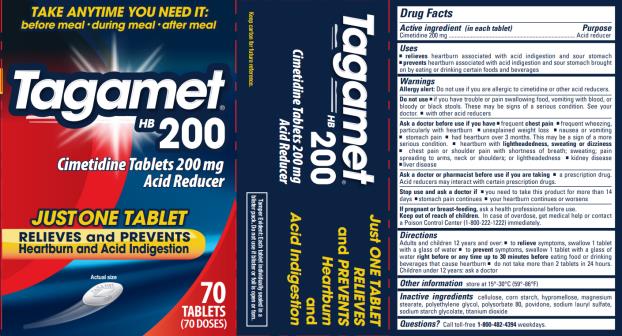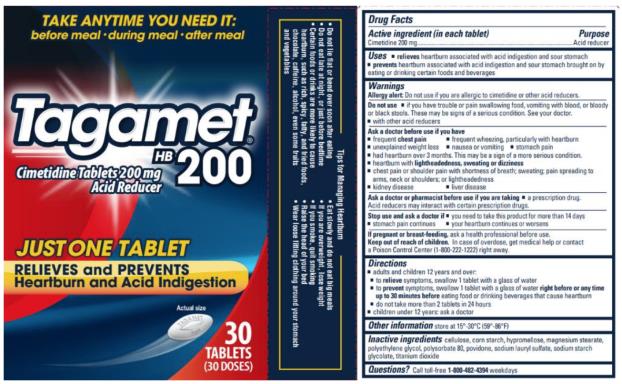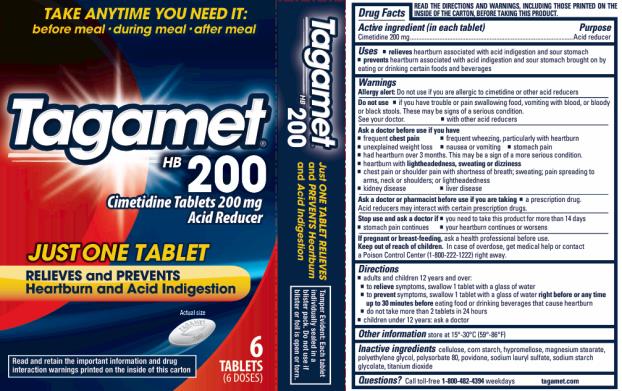 DRUG LABEL: Tagamet
NDC: 63029-222 | Form: TABLET
Manufacturer: Medtech Products Inc.
Category: otc | Type: HUMAN OTC DRUG LABEL
Date: 20240610

ACTIVE INGREDIENTS: CIMETIDINE 200 mg/1 1
INACTIVE INGREDIENTS: STARCH, CORN; HYPROMELLOSES; MAGNESIUM STEARATE; POLYETHYLENE GLYCOL, UNSPECIFIED; POLYSORBATE 80; POVIDONE; SODIUM LAURYL SULFATE; SODIUM STARCH GLYCOLATE TYPE A POTATO; TITANIUM DIOXIDE; MICROCRYSTALLINE CELLULOSE; FD&C BLUE NO. 1 ALUMINUM LAKE

Tagamet

Drug Facts

Active ingredient (in each tablet)

Cimetidine 200mg

Purpose

Acid reducer

Uses

- relieves heartburn associated with acid indigestion and sour stomach
- prevents heartburn associated with acid indigestion and sour stomach brought on by eating or drinking certain foods and beverages

Warnings

Allergy alert: Do not use if you are allergic to cimetidine or other acid reducers.

Do not use

- if you have trouble or pain swallowing food, vomiting with blood, or bloody or black stools. These may be signs of a serious condition. See your doctor.
- with other acid reducers

Ask a doctor before use if you have

- frequent chest pain
- frequent wheezing, particularly with heartburn
- unexplained weight loss
- nausea or vomiting
- stomach pain
- had heartburn over 3 months. This may be a sign of a more serious condition.
- heartburn with lightheadedness, sweating or dizziness
- chest pain or shoulder pain with shortness of breath; sweating; pain spreading to arms, neck or shoulders; or lightheadedness
- kidney disease
- liver disease

Ask a doctor or pharmacist before use if

you are taking a prescription drug.

Acid reducers may interact with certain prescription drugs.

Stop use and ask a doctor if

- you need to take this product for more than 14 days
- stomach pain continues
- your heartburn continues or worsens

If pregnant or breast-feeding,

ask a health professional before use.

Keep out of reach of children.

In case of overdose, get medical help or contact a Poison Control Center (1-800-222-1222) right away.

Directions

- adults and children 12 years and over:
  ▪ to relieve symptoms, swallow 1 tablet with a glass of water
  ▪ to prevent symptoms, swallow 1 tablet with a glass of water right before or any time up to 30 minutes before eating food or drinking beverages that cause heartburn
  ▪ do not take more than 2 tablets in 24 hours
- children under 12 years: ask a doctor

Other information

store at 15-30ºC (59-86ºF)

Inactive ingredients

cellulose, corn starch, hypromellose, magnesium stearate, polyethylene glycol, polysorbate 80, povidone, sodium lauryl sulfate, sodium starch glycolate, titanium dioxide

Questions?

Call toll-free 1-800-482-4394 weekdays

tagamet.com

PRINCIPAL DISPLAY PANEL

Tagamet® HB 200
Cimetidine Tablets 200 mg
Acid Reducer
70 tablets (70 doses)

PRINCIPAL DISPLAY PANEL

Tagamet® HB 200
Cimetidine Tablets 200 mg
Acid Reducer

30 tablets (30 doses)

PRINCIPAL DISPLAY PANEL

Tagamet ® HB 200
Cimetidine Tablets 200 mg
Acid Reducer

6 tablets (6 doses)